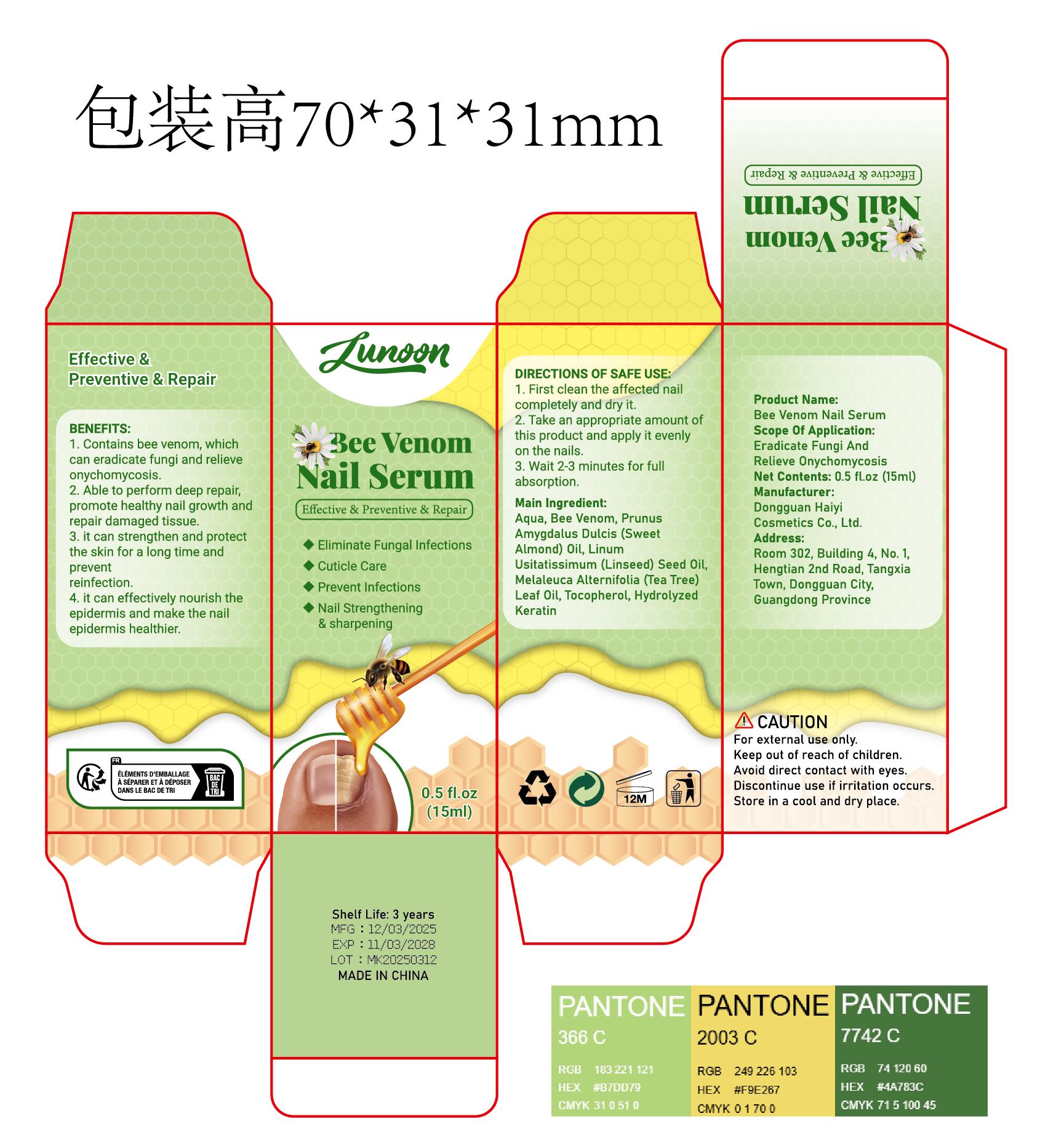 DRUG LABEL: Bee Venom Nail Serum
NDC: 85594-008 | Form: LIQUID
Manufacturer: Dongguan Haiyi Cosmetics Co., Ltd.
Category: otc | Type: HUMAN OTC DRUG LABEL
Date: 20250811

ACTIVE INGREDIENTS: APIS MELLIFERA VENOM 15 mg/100 mL
INACTIVE INGREDIENTS: AQUA; PRUNUS AMYGDALUS DULCIS (SWEET ALMOND) OIL; TOCOPHEROL; COCODIMONIUM HYDROXYPROPYL HYDROLYZED KERATIN (1000 MW); LINUM USITATISSIMUM (LINSEED) SEED OIL; MELALEUCA ALTERNIFOLIA (TEA TREE) LEAF OIL

85594-008-15 Bee Venom Nail Serum

ACTIVE INGREDIENT

APIS MELLIFERA VENOM

INACTIVE INGREDIENT

Aqua, PrunusAmygdalus Dulcis (SweetAlmond) Oil, LinumUsitatissimum (Linseed) Seed Oil,Melaleuca Alternifolia (Tea Tree)Leaf Oil, Tocopherol, HydrolyzedKeratin

PURPOSE

Eliminate Fungal infections

Cuticle Care

Prevent Infections

Nail Strengthening& sharpening

WARNINGS

1).For external use only, avoid directcontact with eyes, lf you feel any
discomfort, stop using itand wash it with plenty of water. In severe cases,
pleaseseek medical attention in time.
2). Not allowed to be used ondamaged skin,

STOP USE

This product may cause allergic reactions in asmall number of people.
lf youexperience any discomfort,please stop using it immediately.

DO NOT USE

Not suitable for use by children, pregnantor breast feeding people.

KEEP OUT OF REACH OF CHILDREN

KEEP THE PRODUCT OUT OF REACH OF CHILDREN to

INDICATIONS AND USAGE

1. First clean the affected nailcompletely and dry it.

2. Take an appropriate amount ofthis product and apply it evenly on the nails.

3. Wait 2-3 minutes for full absorption.

DOSAGE AND ADMINISTRATION

take an appropriateamount,Use 2-3 times a week